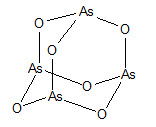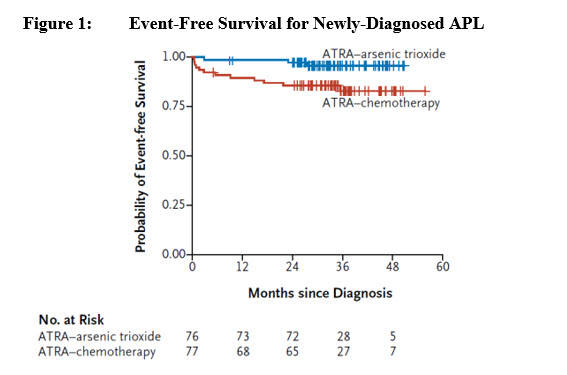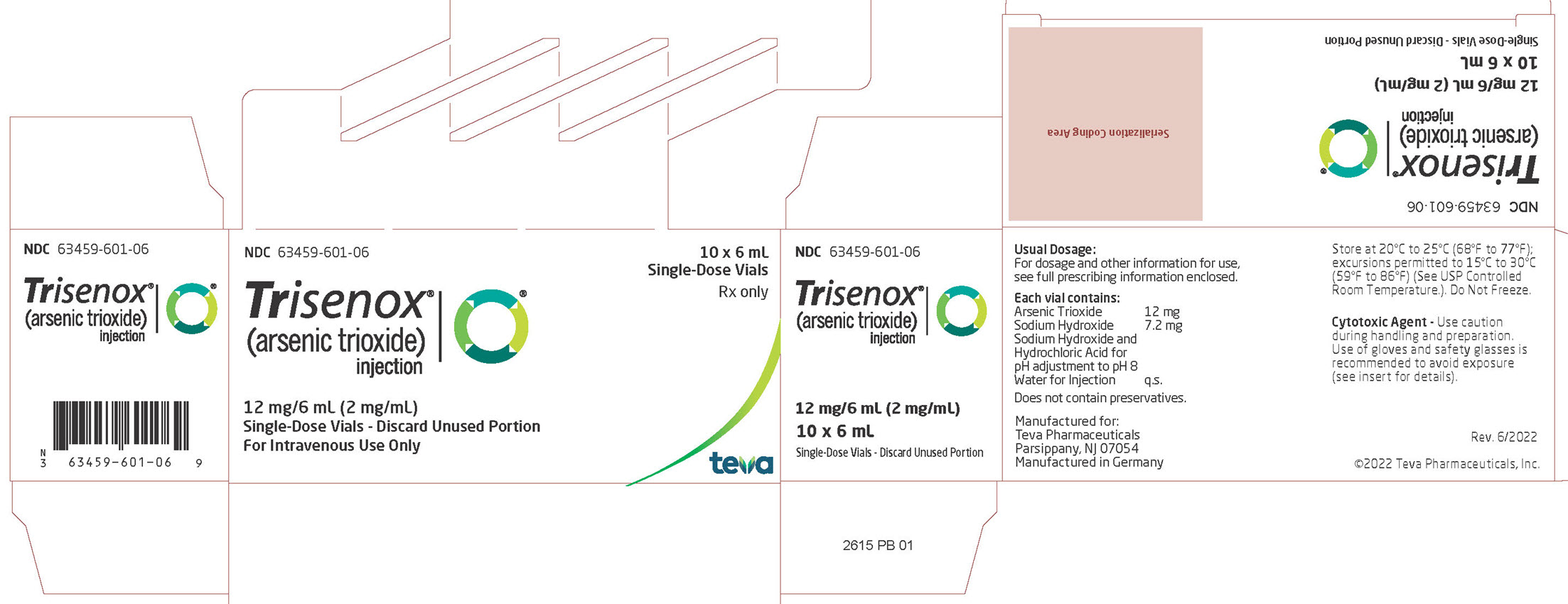 DRUG LABEL: Trisenox
NDC: 63459-601 | Form: INJECTION, SOLUTION
Manufacturer: Cephalon, LLC
Category: prescription | Type: HUMAN PRESCRIPTION DRUG LABEL
Date: 20251028

ACTIVE INGREDIENTS: ARSENIC TRIOXIDE 2 mg/1 mL
INACTIVE INGREDIENTS: WATER; SODIUM HYDROXIDE; HYDROCHLORIC ACID

HIGHLIGHTS OF PRESCRIBING INFORMATION

These highlights do not include all the information needed to use TRISENOX safely and effectively. See full prescribing information for TRISENOX.
TRISENOX® (arsenic trioxide) injection, for intravenous use
Initial U.S. Approval: 2000

WARNING: DIFFERENTIATION SYNDROME, CARDIAC CONDUCTION ABNORMALITIES AND ENCEPHALOPATHY INCLUDING WERNICKE'S

See full prescribing information for complete boxed warning.

- Patients with acute promyelocytic leukemia (APL) treated with TRISENOX have experienced symptoms of differentiation syndrome, which may be life-threatening or fatal. If differentiation syndrome is suspected, immediately initiate high-dose corticosteroids and hemodynamic monitoring until resolution. Temporarily withhold TRISENOX. (2.3, 5.1)
- TRISENOX can cause QTc interval prolongation, complete atrioventricular block and torsade de pointes, which can be fatal. Before administering TRISENOX, assess the QTc interval, correct electrolyte abnormalities, and consider discontinuing drugs known to prolong QTc interval. Do not administer TRISENOX to patients with ventricular arrhythmia or prolonged QTc interval. Withhold TRISENOX until resolution and resume at reduced dose for QTc prolongation. (2.3, 5.2)
- Serious encephalopathy, including Wernicke's, has occurred with TRISENOX. If Wernicke's encephalopathy is suspected, immediately interrupt TRISENOX and initiate parenteral thiamine. Monitor until symptoms resolve or improve and thiamine levels normalize. (5.3)

1 INDICATIONS AND USAGE

TRISENOX is an arsenical indicated:

- In combination with tretinoin for treatment of adults with newly-diagnosed low-risk acute promyelocytic leukemia (APL) whose APL is characterized by the presence of the t(15;17) translocation or PML/RAR-alpha gene expression. (1.1)
- For induction of remission and consolidation in patients with APL who are refractory to, or have relapsed from, retinoid and anthracycline chemotherapy, and whose APL is characterized by the presence of the t(15;17) translocation or PML/RAR-alpha gene expression. (1.2)

2 DOSAGE AND ADMINISTRATION

Newly-diagnosed low-risk APL:

- Induction: Administer 0.15 mg/kg/day intravenously daily in combination with tretinoin until bone marrow remission. Do not exceed 60 days. (2.1)

- Consolidation: Administer 0.15 mg/kg/day intravenously daily for 5 days per week during weeks 1-4 of each 8-week cycle for a total of 4 cycles in combination with tretinoin. (2.1)

Relapsed or refractory APL:

- Induction: Administer 0.15 mg/kg/day intravenously daily until bone marrow remission. Do not exceed 60 days. (2.2)
- Consolidation: Administer 0.15 mg/kg/day intravenously daily for 25 doses over a period of up to 5 weeks. (2.2)

3 DOSAGE FORMS AND STRENGTHS

Injection: 12 mg/6 mL (2 mg/mL) arsenic trioxide in single-dose vial. (3)

4 CONTRAINDICATIONS

Hypersensitivity to arsenic. (4)

5 WARNINGS AND PRECAUTIONS

- Hepatotoxicity: Elevated aspartate aminotransferase (AST), alkaline phosphatase and serum bilirubin have occurred in patients with newly-diagnosed low-risk APL treated with TRISENOX in combination with tretinoin. Monitor hepatic function tests at least twice weekly during induction and at least once weekly during consolidation. Withhold TRISENOX for certain elevations in AST, alkaline phosphatase and bilirubin and resume at reduced dose upon resolution.(2.3, 5.4)
- Carcinogenesis: Arsenic trioxide is a human carcinogen. Monitor patients for the development of second primary malignancies. (5.5)
- Embryo-Fetal Toxicity: Can cause fetal harm. Advise of potential risk to a fetus and use of effective contraception. (5.6, 8.1, 8.3)

6 ADVERSE REACTIONS

The most common adverse reactions (> 30%) are nausea, cough, fatigue, pyrexia, headache, abdominal pain, vomiting, tachycardia, diarrhea, dyspnea, hypokalemia, leukocytosis, hyperglycemia, hypomagnesemia, insomnia, dermatitis, edema, QTc prolongation, rigors, sore throat, arthralgia, paresthesia, and pruritus (6.1).

To report SUSPECTED ADVERSE REACTIONS, contact Teva Pharmaceuticals at 1-888-483-8279 or FDA at 1-800-FDA-1088 or www.fda.gov/medwatch.

8 USE IN SPECIFIC POPULATIONS

- Lactation: Advise not to breastfeed. (8.2)
- Renal Impairment: Monitor patients with severe renal impairment (creatinine clearance less than 30 mL/min) for toxicity when treated with TRISENOX; dose reduction may be warranted. (8.6)
- Hepatic Impairment: Monitor patients with severe hepatic impairment (Child-Pugh Class C) for toxicity when treated with TRISENOX. (8.7)

FULL PRESCRIBING INFORMATION

WARNING: DIFFERENTIATION SYNDROME, CARDIAC CONDUCTION ABNORMALITIES AND ENCEPHALOPATHY INCLUDING WERNICKE'S

Differentiation Syndrome: Patients with acute promyelocytic leukemia (APL) treated with TRISENOX have experienced differentiation syndrome, which may be life-threatening or fatal. Signs and symptoms may include unexplained fever, dyspnea, hypoxia, acute respiratory distress, pulmonary infiltrates, pleural or pericardial effusions, weight gain, peripheral edema, hypotension, renal insufficiency, hepatopathy, and multi-organ dysfunction, in the presence or absence of leukocytosis. If differentiation syndrome is suspected, immediately initiate high-dose corticosteroids and hemodynamic monitoring until resolution. Temporarily withhold TRISENOX [see Dosage and Administration (2.3), Warnings and Precautions (5.1)].

Cardiac Conduction Abnormalities: TRISENOX can cause QTc interval prolongation, complete atrioventricular block and torsade de pointes, which can be fatal. Before administering TRISENOX, assess the QTc interval, correct electrolyte abnormalities, and consider discontinuing drugs known to prolong QTc interval. Do not administer TRISENOX to patients with a ventricular arrhythmia or prolonged QTc interval. Withhold TRISENOX until resolution and resume at reduced dose for QTc prolongation [see Dosage and Administration (2.3), Warnings and Precautions (5.2)].

Encephalopathy: Serious encephalopathy, including Wernicke's, has occurred with TRISENOX. Wernicke's is a neurologic emergency. Consider testing thiamine levels in patients at risk for thiamine deficiency. Administer parenteral thiamine in patients with or at risk for thiamine deficiency. Monitor patients for neurological symptoms and nutritional status while receiving TRISENOX. If Wernicke's encephalopathy is suspected, immediately interrupt TRISENOX and initiate parenteral thiamine. Monitor until symptoms resolve or improve and thiamine levels normalize [see Warnings and Precautions (5.3)].

1 INDICATIONS AND USAGE

1.1 Newly-Diagnosed Low-Risk APL

TRISENOX is indicated in combination with tretinoin for treatment of adults with newly-diagnosed low-risk acute promyelocytic leukemia (APL) whose APL is characterized by the presence of the t(15;17) translocation or PML/RAR-alpha gene expression.

1.2 Relapsed or Refractory APL

TRISENOX is indicated for induction of remission and consolidation in patients with APL who are refractory to, or have relapsed from, retinoid and anthracycline chemotherapy, and whose APL is characterized by the presence of the t(15;17) translocation or PML/RAR-alpha gene expression.

2 DOSAGE AND ADMINISTRATION

2.1 Recommended Dosage for Newly-Diagnosed Low-Risk Acute Promyelocytic Leukemia (APL)

A treatment course for patients with newly-diagnosed low-risk APL consists of 1 induction cycle and 4 consolidation cycles.

- For the induction cycle, the recommended dosage of TRISENOX is 0.15 mg/kg/day intravenously daily in combination with tretinoin until bone marrow remission but not to exceed 60 days (see Table 1).

- For the consolidation cycles, the recommended dosage of TRISENOX is 0.15 mg/kg/day intravenously daily 5 days per week during weeks 1-4 of each 8-week cycle for a total of 4 cycles in combination with tretinoin (see Table 1). Omit tretinoin during weeks 5-6 of the fourth cycle of consolidation.

Table 1: Recommended Dosage of TRISENOX in Combination with Tretinoin

Induction (1 cycle)
TRISENOX; 0.15 mg/kg once daily intravenously | until marrow remission but not to exceed 60 days
Tretinoina; 22.5 mg/m^2 twice daily orally | until marrow remission but not to exceed 60 days
Consolidation (4 cycles)
 | Week 1 | Week 2 | Week 3 | Week 4 | Week 5 | Week 6 | Week 7 | Week 8
TRISENOX; 0.15 mg/kg once; daily intravenously | Days 1-5 | Days 1-5 | Days 1-5 | Days 1-5 | -- | -- | -- | --
Tretinoina; 22.5 mg/m^2 twice daily orally | Days 1-7 | Days 1-7 | -- | -- | Daysb 1-7 | Daysb 1-7 | -- | --
a Rounded to the nearest 10 mg increment
b Omitted during the 4th cycle of consolidation

Differentiation syndrome prophylaxis consisting of prednisone 0.5 mg/kg daily from day 1 until the end of induction cycle with TRISENOX and tretinoin is recommended.

2.2 Recommended Dosage for Relapsed or Refractory APL

A treatment course for patients with relapsed or refractory APL consists of 1 induction cycle and 1 consolidation cycle [see Clinical Studies (14.2)].

- For the induction cycle, the recommended dosage of TRISENOX is 0.15 mg/kg/day intravenously daily until bone marrow remission or up to a maximum of 60 days.
- For the consolidation cycle, the recommended dosage of TRISENOX is 0.15 mg/kg/day intravenously daily for 25 doses over a period of up to 5 weeks. Begin consolidation 3 to 6 weeks after completion of induction cycle.

2.3 Monitoring and Dosage Modifications for Adverse Reactions

During induction, monitor coagulation studies, blood counts, and chemistries at least 2-3 times per week through recovery. During consolidation, monitor coagulation studies, blood counts, and chemistries at least weekly.

Table 2 shows the dosage modifications for adverse reactions due to TRISENOX when used alone or in combination with tretinoin.

Table 2: Dosage Modifications for Adverse Reactions of TRISENOX

Adverse Reaction | Dosage Modification
Differentiation syndrome, defined by the presence of 2 or more of the following:; - Unexplained fever - Dyspnea - Pleural and/or pericardial effusion - Pulmonary infiltrates - Renal failure - Hypotension - Weight gain greater than 5 kg; [see Warnings and Precautions (5.1)] | - Temporarily withhold TRISENOX. Consider holding tretinoin if symptoms are severe. - Administer dexamethasone 10 mg intravenously every 12 hours until the resolution of signs and symptoms for a minimum of 3 days. - Resume treatment when the clinical condition improves and reduce the dose of the withheld drug(s) by 50%. - Increase the dose of the withheld drug(s) to the recommended dosage after one week in the absence of recurrence of symptoms of differentiation syndrome. - If symptoms re-appear, decrease TRISENOX and/or tretinoin to the previous dose.
QTc (Framingham formula) Prolongation greater than 450 msec for men or greater than 460 msec for women [see Warnings and Precautions (5.2)] | - Withhold TRISENOX and any medication known to prolong the QTc interval. - Correct electrolyte abnormalities. - After the QTc normalizes and electrolyte abnormalities are corrected, resume treatment with TRISENOX at a 50% reduced dose (0.075 mg/kg/day daily) for one week after resolution. - If the 50% reduced dose is tolerated for one week (in the absence of QTc prolongation), increase the dose of TRISENOX to 0.11 mg/kg/day daily for the next week [see Dosage and Administration (2.1)]. - The dose of TRISENOX can be increased to 0.15 mg/kg/day in the absence of QTc prolongation during that 14-day dose-escalation period.
Hepatotoxicity, defined by 1 or more of the following:; - Total bilirubin (TB) greater than 3 times the upper limit of normal (ULN) - Aspartate aminotransferase (AST) greater than 5 times the ULN - Alkaline phosphatase (AP) greater than 5 times the ULN; [see Warnings and Precautions (5.4)] | - Withhold TRISENOX and/or tretinoin. - Resume treatment at a 50% reduced dose of the withheld drug(s) when TB is less than 1.5 times the ULN and AP/AST are less than 3 times the ULN. - Increase the dose of the withheld drug(s) back to the recommended dosage after one week on the reduced dose in the absence of worsening of hepatotoxicity. - Discontinue the withheld drug(s) permanently if hepatotoxicity recurs.
Other severe or life-threatening (grade 3-4) nonhematologic reactions [see Adverse Reactions (6)] | - Temporarily withhold TRISENOX and tretinoin. - When the adverse reaction resolves to no more than mild (grade 1), resume TRISENOX and tretinoin reduced by 2 dose levels (see Table 3 below).
Moderate (grade 2) nonhematologic reactions; [see Adverse Reactions (6)] | - Reduce the dose of TRISENOX and/or tretinoin by 1 dose level (see Table 3 below).
Leukocytosis (WBC count greater than 10 Gi/L); [see Adverse Reactions (6.1)] | - Administer hydroxyurea. - Hydroxyurea may be discontinued when the WBC declines below 10 Gi/L.
Myelosuppression, defined by 1 or more of the following:; - absolute neutrophil count less than 1 Gi/L - platelets less than 50 Gi/L lasting more than 5 weeks; [see Adverse Reactions (6)] | - Consider reducing the dose of TRISENOX and tretinoin by 1 dose level (see Table 3 below). - If myelosuppression lasts ≥ 50 days or occurs on 2 consecutive cycles, assess a marrow aspirate for remission status. In the case of molecular remission, resume TRISENOX and tretinoin at 1 dose level lower (see Table 3 below).

Table 3: Dose Reduction Levels for Hematologic and Nonhematologic Toxicities

Dose Level | TRISENOX mg/kg intravenously once daily | Tretinoin* mg/m^2 orally twice daily
Starting level | 0.15 | 22.5
-1 | 0.11 | 18.75
-2 | 0.10 | 12.5
-3 | 0.075 | 10

*Rounded to the nearest 10 mg increment

2.4 Preparation and Administration

Reconstitution

Dilute TRISENOX with 100 to 250 mL 5% Dextrose Injection, USP or 0.9% Sodium Chloride Injection, USP, using proper aseptic technique, immediately after withdrawal from the vial. Do not save any unused portions for later administration.

After dilution, store TRISENOX for no more than 24 hours at room temperature and 48 hours when refrigerated.

Administration

Parenteral drug products should be inspected visually for particulate matter and discoloration prior to administration, whenever solution and container permit.

Administer TRISENOX as an intravenous infusion over 2 hours. The infusion duration may be extended up to 4 hours if acute vasomotor reactions are observed. A central venous catheter is not required.

The TRISENOX vial is single-dose and does not contain any preservatives. Discard unused portions of each vial properly. Do not mix TRISENOX with other medications.

Safe Handling Procedures

TRISENOX is a hazardous drug. Follow applicable special handling and disposal procedures.^1

3 DOSAGE FORMS AND STRENGTHS

Injection: 12 mg/6 mL (2 mg/mL) arsenic trioxide clear solution in a single-dose vial

4 CONTRAINDICATIONS

TRISENOX is contraindicated in patients with hypersensitivity to arsenic.

5 WARNINGS AND PRECAUTIONS

5.1 Differentiation Syndrome

Differentiation syndrome, which may be life-threatening or fatal, has been observed in patients with acute promyelocytic leukemia (APL) treated with TRISENOX. In clinical trials, 16-23% of patients treated with TRISENOX for APL developed differentiation syndrome. Signs and symptoms include unexplained fever, dyspnea, hypoxia, acute respiratory distress, pulmonary infiltrates, pleural or pericardial effusion, weight gain, peripheral edema, hypotension, renal insufficiency, hepatopathy and multi-organ dysfunction. Differentiation syndrome has been observed with and without concomitant leukocytosis, and it has occurred as early as day 1 of induction to as late as the second month induction therapy.

When TRISENOX is used in combination with tretinoin, prophylaxis with prednisone is recommended during the induction cycle [see Dosage and Administration (2.1)].

If differentiation syndrome is suspected, temporarily withhold TRISENOX and immediately initiate dexamethasone 10 mg intravenously every 12 hours and hemodynamic monitoring until resolution of signs and symptoms for a minimum of 3 days [see Dosage and Administration (2.3)].

5.2 Cardiac Conduction Abnormalities

Patients treated with TRISENOX can develop QTc prolongation, torsade de pointes, and complete atrioventricular block. In the clinical trials of patients with newly-diagnosed low-risk APL treated with TRISENOX in combination with tretinoin, 11% experienced QTc (Framingham formula) prolongation > 450 msec for men and > 460 msec for women throughout the treatment cycles. In the clinical trial of patients with relapsed or refractory APL treated with TRISENOX monotherapy, 40% had at least one ECG tracing with a QTc interval greater than 500 msec. A prolonged QTc was observed between 1 and 5 weeks after start of TRISENOX infusion, and it usually resolved by 8 weeks after TRISENOX infusion. There are no data on the effect of TRISENOX on the QTc interval during the infusion of the drug.

The risk of torsade de pointes is related to the extent of QTc prolongation, concomitant administration of QTc prolonging drugs, a history of torsade de pointes, pre-existing QTc interval prolongation, congestive heart failure, administration of potassium-wasting diuretics, or other conditions that result in hypokalemia or hypomagnesemia. The risk may be increased when TRISENOX is coadministered with medications that can lead to electrolyte abnormalities (such as diuretics or amphotericin B) [see Drug Interactions (7)].

Prior to initiating therapy with TRISENOX, assess the QTc interval by electrocardiogram, correct pre-existing electrolyte abnormalities, and consider discontinuing drugs known to prolong QTc interval. Do not administer TRISENOX to patients with a ventricular arrhythmia or prolonged QTc. If possible, discontinue drugs that are known to prolong the QTc interval. If it is not possible to discontinue the interacting drug, perform cardiac monitoring frequently [see Drug Interactions (7)]. During TRISENOX therapy, maintain potassium concentrations above 4 mEq/L and magnesium concentrations above 1.8 mg/dL. Monitor ECG weekly and more frequently for clinically unstable patients.

For patients who develop a QTc Framingham greater than 450 msec for men or greater than 460 msec for women, withhold TRISENOX and any medication known to prolong the QTc interval. Correct electrolyte abnormalities. When the QTc normalizes and electrolyte abnormalities are corrected, resume TRISENOX at a reduced dose [see Dosage and Administration (2.3)].

5.3 Encephalopathy

Serious encephalopathies were reported in patients receiving TRISENOX. Monitor patients for neurological symptoms, such as confusion, decreased level of consciousness, seizures, cognitive deficits, ataxia, visual symptoms and ocular motor dysfunction. Advise patients and caregivers of the need for close observation.

Wernicke’s Encephalopathy

Wernicke’s encephalopathy occurred in patients receiving TRISENOX. Wernicke’s encephalopathy is a neurologic emergency that can be prevented and treated with thiamine. Consider testing thiamine levels in patients at risk for thiamine deficiency (e.g., chronic alcohol use, malabsorption, nutritional deficiency, concomitant use of furosemide). Administer parenteral thiamine in patients with or at risk for thiamine deficiency. Monitor patients for neurological symptoms and nutritional status while receiving TRISENOX. If Wernicke’s encephalopathy is suspected, immediately interrupt TRISENOX and initiate parenteral thiamine. Monitor until symptoms resolve or improve and thiamine levels normalize.

5.4 Hepatotoxicity

In the clinical trials, 44% of patients with newly-diagnosed low-risk APL treated with TRISENOX in combination with tretinoin experienced elevated aspartate aminotransferase (AST), alkaline phosphatase, and/or serum bilirubin. These abnormalities resolved with temporary discontinuation of TRISENOX and/or tretinoin.

Long-term liver abnormalities can occur in patients with APL treated with TRISENOX in combination with tretinoin. In a published series, mild liver dysfunction and hepatic steatosis were seen in 15% and 43%, respectively, of patients at a median of 7 years (range 0 to 14 years) after treatment with arsenic trioxide in combination with tretinoin.

During treatment with TRISENOX, monitor hepatic function tests at least twice weekly during induction and at least once weekly during consolidation. Withhold TRISENOX and/or tretinoin if elevations in AST or alkaline phosphatase occur to greater than 5 times the upper limit of normal and/or elevation in serum total bilirubin occurs to greater than 3 times the upper limit of normal and resume at reduced dose upon resolution [see Dosage and Administration (2.3)].

5.5 Carcinogenesis

The active ingredient of TRISENOX, arsenic trioxide, is a human carcinogen. Monitor patients for the development of second primary malignancies.

5.6 Embryo-Fetal Toxicity

TRISENOX can cause fetal harm when administered to a pregnant woman. Arsenic trioxide was embryolethal and teratogenic in rats when administered on gestation day 9 at a dose approximately 10 times the recommended human daily dose on a mg/m^2 basis. A related trivalent arsenic, sodium arsenite, produced teratogenicity when administered during gestation in mice at a dose approximately 5 times the projected human dose on a mg/m^2 basis and in hamsters at an intravenous dose approximately equivalent to the projected human daily dose on a mg/m^2 basis.

Advise pregnant women of the potential risk to a fetus. Advise females of reproductive potential to use effective contraception during treatment with TRISENOX and for 6 months after the last dose. Advise males with female partners of reproductive potential to use effective contraception during treatment with TRISENOX and for 3 months after the last dose [see Use in Specific Populations (8.1, 8.3)].

6 ADVERSE REACTIONS

The following clinically significant adverse reactions are described elsewhere in the labeling:

- Differentiation Syndrome [see Warnings and Precautions (5.1)]
- Cardiac Conduction Abnormalities [see Warnings and Precautions (5.2)]
- Encephalopathy [see Warnings and Precautions (5.3)]
- Hepatotoxicity [see Warnings and Precautions (5.4)]
- Carcinogenesis [see Warnings and Precautions (5.5)]

6.1 Clinical Trials Experience

Because clinical trials are conducted under widely varying conditions, adverse reaction rates observed in the clinical trials of a drug cannot be directly compared to rates in the clinical trials of another drug and may not reflect the rates observed in practice.

Newly-Diagnosed Low-Risk APL

The safety of TRISENOX in combination with tretinoin was evaluated in Study APL0406, a randomized trial comparing TRISENOX plus tretinoin (n=129) versus chemotherapy plus tretinoin (n=137) in patients with newly-diagnosed APL [see Clinical Studies (14.1)]. In the TRISENOX/tretinoin group, 98% of patients completed induction therapy and 89% completed at least three consolidation cycles. In the chemotherapy/tretinoin group, 96% completed induction therapy and 87% patients completed all three courses of consolidation therapy.

Serious adverse reactions were reported in 25% of patients on the TRISENOX/tretinoin arm and 24% on the chemotherapy/tretinoin arm. The serious adverse reactions reported in ≥ 2% of patients who received TRISENOX/tretinoin were abnormal liver tests, differentiation syndrome, dyspnea, pneumonia, and other infections. Fatal adverse reactions were reported in 1 (1%) patient on the TRISENOX/tretinoin arm and 8 (6%) patients on the chemotherapy/tretinoin arm.

TRISENOX/tretinoin was discontinued due to toxicity in 1 patient during induction and in 4 patients during the first three consolidation courses, whereas chemotherapy/tretinoin was discontinued due to toxicity in 4 patients during induction and in 6 patients during consolidation.

Selected hematologic and nonhematologic toxicities that occurred during induction or consolidation are presented in Table 4.

Table 4: Select Adverse Reactions of Trisenox in Combination with Tretinoin in Patients with Newly-Diagnosed APL in Study APL0406

 | Induction | First Consolidation | Second Consolidation | Third Consolidation
Adverse Reaction | n (%) | n (%) | n (%) | n (%)
Thrombocytopenia > 15 days (Grade 3-4)
TRISENOX/tretinoin | 74 (58%) | 6 (5%) | 6 (5%) | 8 (7%)
Chemotherapy/tretinoin | 120 (88%) | 17 (14%) | 77 (63%) | 26 (22%)
Neutropenia >15 days (Grade 3-4)
TRISENOX/tretinoin | 61 (48%) | 8 (7%) | 7 (6%) | 5 (4%)
Chemotherapy/tretinoin | 109 (80%) | 40 (32%) | 90 (73%) | 28 (24%)
Hepatic toxicity (Grade 3-4)
TRISENOX/tretinoin | 51 (40%) | 5 (4%) | 1 (1%) | 0 (0%)
Chemotherapy/tretinoin | 4 (3%) | 1 (1%) | 0 (0%) | 0 (0%)
Infection and fever of unknown origin
TRISENOX/tretinoin | 30 (23%) | 10 (8%) | 4 (3%) | 2 (2%)
Chemotherapy/tretinoin | 75 (55%) | 8 (6%) | 46 (38%) | 2 (2%)
Hypertriglyceridemia
TRISENOX/tretinoin | 29 (22%) | 22 (18%) | 17 (14%) | 16 (14%)
Chemotherapy/tretinoin | 29 (22%) | 19 (15%) | 10 (8%) | 13 (11%)
Hypercholesterolemia
TRISENOX/tretinoin | 14 (10%) | 19 (16%) | 19 (16%) | 16 (14%)
Chemotherapy/tretinoin | 12 (9%) | 12 (10%) | 12 (10%) | 11 (9%)
QT prolongation
TRISENOX/tretinoin | 11 (9%) | 3 (2%) | 3 (2%) | 2 (2%)
Chemotherapy/tretinoin | 1 (1%) | 0 (0%) | 0 (0%) | 0 (0%)
Gastrointestinal toxicity (Grade 3-4)
TRISENOX/tretinoin | 3 (2%) | 0 (0%) | 0 (0%) | 0 (0%)
Chemotherapy/tretinoin | 25 (18%) | 1 (1%) | 6 (5%) | 0 (0%)
Neurotoxicity*
TRISENOX/tretinoin | 1 (1%) | 5 (4%) | 6 (5%) | 7 (6%)
Chemotherapy/tretinoin | 0 (0%) | 0 (0%) | 0 (0%) | 0 (0%)
Cardiac function (Grade 3-4)
TRISENOX/tretinoin | 0 (0%) | 0 (0%) | 0 (0%) | 0 (0%)
Chemotherapy/tretinoin | 5 (4%) | 0 (0%) | 0 (0%) | 0 (0%)

*Mostly cases of reversible peripheral neuropathy

Relapsed or Refractory APL

Safety information was available for 52 patients with relapsed or refractory APL who participated in clinical trials of TRISENOX. Forty patients in the Study PLRXAS01 received the recommended dose of 0.15 mg/kg, of whom 28 completed both induction and consolidation cycles. An additional 12 patients with relapsed or refractory APL received doses generally similar to the recommended dose.

Serious adverse reactions observed in the 40 patients with refractory or relapsed APL enrolled in Study PLRXAS01 included differentiation syndrome (n=3), hyperleukocytosis (n=3), QTc interval ≥ 500 msec (n=16, 1 with torsade de pointes), atrial dysrhythmias (n=2), and hyperglycemia (n=2).

The most common adverse reactions (> 30%) were nausea, cough, fatigue, pyrexia, headache, abdominal pain, vomiting, tachycardia, diarrhea, dyspnea, hypokalemia, leukocytosis, hyperglycemia, hypomagnesemia, insomnia, dermatitis, edema, QTc prolongation, rigors, sore throat, arthralgia, paresthesia, and pruritus.

Table 5 describes the adverse reactions in patients aged 5 to 73 years with APL who received TRISENOX at the recommended dose. Similar adverse reactions profiles were seen in the other patient populations who received TRISENOX.

Table 5: Adverse Reactions (≥ 5%) in Patients with Relapsed or Refractory APL Who Received TRISENOX in Study PLRXAS01

Body System Adverse reaction | Any Grade Adverse Reactions |  | Grade ≥3 Adverse Reactions
Body System Adverse reaction | n | % | n | %
Gastrointestinal disorders
Nausea | 30 | 75
Abdominal pain (lower & upper) | 23 | 58 | 4 | 10
Vomiting | 23 | 58
Diarrhea | 21 | 53
Sore throat | 14 | 35
Constipation | 11 | 28 | 1 | 3
Anorexia | 9 | 23
Appetite decreased | 6 | 15
Loose stools | 4 | 10
Dyspepsia | 4 | 10
Oral blistering | 3 | 8
Fecal incontinence | 3 | 8
Gastrointestinal hemorrhage | 3 | 8
Dry mouth | 3 | 8
Abdominal tenderness | 3 | 8
Diarrhea hemorrhagic | 3 | 8
Abdominal distension | 3 | 8
Respiratory
Cough | 26 | 65
Dyspnea | 21 | 53 | 4 | 10
Epistaxis | 10 | 25
Hypoxia | 9 | 23 | 4 | 10
Pleural effusion | 8 | 20 | 1 | 3
Post nasal drip | 5 | 13
Wheezing | 5 | 13
Decreased breath sounds | 4 | 10
Crepitations | 4 | 10
Rales | 4 | 10
Hemoptysis | 3 | 8
Tachypnea | 3 | 8
Rhonchi | 3 | 8
General disorders and administration site conditions
Fatigue | 25 | 63 | 2 | 5
Pyrexia (fever) | 25 | 63 | 2 | 5
Edema - non-specific | 16 | 40
Rigors | 15 | 38
Chest pain | 10 | 25 | 2 | 5
Injection site pain | 8 | 20
Pain - non-specific | 6 | 15 | 1 | 3
Injection site erythema | 5 | 13
Weight gain | 5 | 13
Injection site edema | 4 | 10
Weakness | 4 | 10 | 2 | 5
Hemorrhage | 3 | 8
Weight loss | 3 | 8
Drug hypersensitivity | 2 | 5 | 1 | 3
Nervous system disorders
Headache | 24 | 60 | 1 | 3
Insomnia | 17 | 43 | 1 | 3
Paresthesia | 13 | 33 | 2 | 5
Dizziness (excluding vertigo) | 9 | 23
Tremor | 5 | 13
Convulsion | 3 | 8 | 2 | 5
Somnolence | 3 | 8
Coma | 2 | 5 | 2 | 5
Cardiac disorders
Tachycardia | 22 | 55
ECG QT corrected interval prolonged; > 500 msec | 16 | 40
Palpitations | 4 | 10
ECG abnormal other than QT interval prolongation | 3 | 8
Metabolism and nutrition disorders
Hypokalemia | 20 | 50 | 5 | 13
Hypomagnesemia | 18 | 45 | 5 | 13
Hyperglycemia | 18 | 45 | 5 | 13
ALT increased | 8 | 20 | 2 | 5
Hyperkalemia | 7 | 18 | 2 | 5
AST increased | 5 | 13 | 1 | 3
Hypocalcemia | 4 | 10
Hypoglycemia | 3 | 8
Acidosis | 2 | 5
Hematologic disorders
Leukocytosis | 20 | 50 | 1 | 3
Anemia | 8 | 20 | 2 | 5
Thrombocytopenia | 7 | 18 | 5 | 13
Febrile neutropenia | 5 | 13 | 3 | 8
Neutropenia | 4 | 10 | 4 | 10
Disseminated intravascular coagulation | 3 | 8 | 3 | 8
Lymphadenopathy | 3 | 8
Skin and subcutaneous tissue disorders
Dermatitis | 17 | 43
Pruritus | 13 | 33 | 1 | 3
Ecchymosis | 8 | 20
Dry skin | 6 | 15
Erythema - non-specific | 5 | 13
Increased sweating | 5 | 13
Facial edema | 3 | 8
Night sweats | 3 | 8
Petechiae | 3 | 8
Hyperpigmentation | 3 | 8
Non-specific skin lesions | 3 | 8
Urticaria | 3 | 8
Local exfoliation | 2 | 5
Eyelid edema | 2 | 5
Musculoskeletal, connective tissue, and bone disorders
Arthralgia | 13 | 33 | 3 | 8
Myalgia | 10 | 25 | 2 | 5
Bone pain | 9 | 23 | 4 | 10
Back pain | 7 | 18 | 1 | 3
Neck pain | 5 | 13
Pain in limb | 5 | 13 | 2 | 5
Psychiatric disorders
Anxiety | 12 | 30
Depression | 8 | 20
Agitation | 2 | 5
Confusion | 2 | 5
Vascular disorders
Hypotension | 10 | 25 | 2 | 5
Flushing | 4 | 10
Hypertension | 4 | 10
Pallor | 4 | 10
Infections and infestations
Sinusitis | 8 | 20
Herpes simplex | 5 | 13
Upper respiratory tract infection | 5 | 13 | 1 | 3
Bacterial infection - non-specific | 3 | 8 | 1 | 3
Herpes zoster | 3 | 8
Nasopharyngitis | 2 | 5
Oral candidiasis | 2 | 5
Sepsis | 2 | 5 | 2 | 5
Reproductive system disorders
Vaginal hemorrhage | 5 | 13
Intermenstrual bleeding | 3 | 8
Ocular disorders
Eye irritation | 4 | 10
Blurred vision | 4 | 10
Dry eye | 3 | 8
Painful red eye | 2 | 5
Renal and urinary disorders
Renal failure | 3 | 8 | 1 | 3
Renal impairment | 3 | 8
Oliguria | 2 | 5
Incontinence | 2 | 5
Ear disorders
Earache | 3 | 8
Tinnitus | 2 | 5

Other Clinically Relevant Adverse Reactions

Leukocytosis

TRISENOX can induce proliferation of leukemic promyelocytes resulting in a rapid increase in white blood cell count. Leukocytosis greater than 10 Gi/L developed during induction therapy in 43% patients receiving TRISENOX/tretinoin for newly-diagnosed low-risk APL and in 50% of patients receiving TRISENOX monotherapy for relapsed/refractory APL. In the relapsed/refractory setting, a relationship did not exist between baseline WBC counts and development of hyperleukocytosis nor baseline WBC counts and peak WBC counts.

6.2 Postmarketing Experience

The following adverse reactions have been identified during postapproval use of TRISENOX. Because these reactions are reported voluntarily from a population of uncertain size, it is not always possible to reliably estimate the frequency or establish a causal relationship to drug exposure.

Cardiac disorders: Ventricular extrasystoles in association with QT prolongation, ventricular tachycardia in association with QT prolongation, including torsade de pointes, atrioventricular block, and congestive heart failure

Ear and labyrinth disorders: Deafness

Hematologic disorders: Pancytopenia, bone marrow necrosis

Infections: Herpes zoster

Investigations: Gamma-glutamyltransferase increased

Musculoskeletal and connective tissue disorders: Bone pain, myalgia, rhabdomyolysis

Neoplasms benign, malignant and unspecified: Melanoma, pancreatic cancer, squamous cell carcinoma

Nervous system disorders: Peripheral neuropathy, paresis, seizures, confusion, encephalopathy, Wernicke's encephalopathy, posterior reversible encephalopathy syndrome

Skin and subcutaneous tissue disorders: Toxic epidermal necrolysis

7 DRUG INTERACTIONS

Drugs That Can Prolong the QT/QTc Interval

Concomitant use of these drugs and TRISENOX may increase the risk of serious QT/QTc interval prolongation [see Warnings and Precautions (5.1)]. Discontinue or replace with an alternative drug that does not prolong the QT/QTc interval while the patient is using TRISENOX. Monitor ECGs more frequently in patients when it is not feasible to avoid concomitant use.

Drugs That Can Lead to Electrolyte Abnormalities

Electrolyte abnormalities increase the risk of serious QT/QTc interval prolongation [see Warnings and Precautions (5.1)]. Avoid concomitant use of drugs that can lead to electrolyte abnormalities. Monitor electrolytes more frequently in patients who must receive concomitant use of these drugs and TRISENOX.

Drugs That Can Lead to Hepatotoxicity

Concomitant use of these drugs and TRISENOX, particularly when given in combination with tretinoin, may increase the risk of serious hepatotoxicity [see Warnings and Precautions (5.4)]. Discontinue or replace with an alternative drug that does not cause hepatotoxicity while the patient is using TRISENOX. Monitor liver function tests more frequently in patients when it is not feasible to avoid concomitant use.

8 USE IN SPECIFIC POPULATIONS

8.1 Pregnancy

Risk Summary

Based on the mechanism of action [see Clinical Pharmacology (12.1)] and findings in animal studies, TRISENOX can cause fetal harm when administered to a pregnant woman. Arsenic trioxide was embryolethal and teratogenic in rats when administered on gestation day 9 at a dose approximately 10 times the recommended human daily dose on a mg/m^2 basis (see Data). A related trivalent arsenic, sodium arsenite, produced teratogenicity when administered during gestation in mice at a dose approximately 5 times the projected human dose on a mg/m^2 basis and in hamsters at an intravenous dose approximately equivalent to the projected human daily dose on a mg/m^2 basis. There are no studies with the use of TRISENOX in pregnant women, and limited published data on arsenic trioxide use during pregnancy are insufficient to inform a drug-associated risk of major birth defects and miscarriage. Advise pregnant women of the potential risk to a fetus.

The estimated background risk of major birth defects and miscarriage for the indicated population is unknown. All pregnancies have a background risk of birth defect, loss, or other adverse outcomes. In the U.S. general population, the estimated background risk of major birth defects and miscarriage in clinically recognized pregnancies is 2% to 4% and 15% to 20%, respectively.

Data

Human Data

One patient was reported to deliver a live infant with no reported congenital anomalies after receiving arsenic trioxide during the first five months of pregnancy. A second patient became pregnant three months after discontinuing arsenic trioxide and was reported to have a normal pregnancy outcome. A third patient was a pregnant healthcare provider who experienced dermal contact with liquid arsenic trioxide and had a normal pregnancy outcome after treatment and monitoring. A fourth patient who became pregnant while receiving arsenic trioxide had a miscarriage.

Animal Data

Studies in pregnant mice, rats, hamsters, and primates have shown that inorganic arsenicals cross the placental barrier when given orally or by injection. An increase in resorptions, neural-tube defects, anophthalmia and microphthalmia were observed in rats administered 10 mg/kg of arsenic trioxide on gestation day 9 (approximately 10 times the recommended human daily dose on a mg/m^2 basis). Similar findings occurred in mice administered a 10 mg/kg dose of a related trivalent arsenic, sodium arsenite (approximately 5 times the projected human dose on a mg/m^2 basis), on gestation days 6, 7, 8, or 9. Intravenous injection of 2 mg/kg sodium arsenite (approximately equivalent to the projected human daily dose on a mg/m^2 basis) on gestation day 7 (the lowest dose tested) resulted in neural-tube defects in hamsters.

8.2 Lactation

Risk Summary

Arsenic trioxide is excreted in human milk. There are no data on the effects of arsenic trioxide on the breastfed child or on milk production. Because of the potential for serious adverse reactions in a breastfed child, advise women not to breastfeed during treatment with TRISENOX and for 2 weeks after the final dose.

8.3 Females and Males of Reproductive Potential

TRISENOX can cause fetal harm when administered to a pregnant woman [see Use in Specific Populations (8.1)].

Pregnancy Testing

Conduct pregnancy testing in females of reproductive potential prior to initiation of TRISENOX.

Contraception

Females

Advise females of reproductive potential to use effective contraception during treatment with TRISENOX and for 6 months after the final dose.

Males

Advise males with female partners of reproductive potential to use effective contraception during treatment with TRISENOX and for 3 months after the final dose.

Infertility

Males

Based on testicular toxicities including decreased testicular weight and impaired spermatogenesis observed in animal studies, TRISENOX may impair fertility in males of reproductive potential [see Nonclinical Toxicology (13.1)].

8.4 Pediatric Use

The safety and efficacy of TRISENOX in combination with tretinoin in pediatric patients has not been established.

The safety and efficacy of TRISENOX as a single agent for treatment of pediatric patients with relapsed or refractory APL is supported by the pivotal phase 2 study in 40 patients with relapsed or refractory APL. Five patients below the age of 18 years (age range: 5 to 16 years) were treated with TRISENOX at the recommended dose of 0.15 mg/kg/day. A literature review included an additional 17 patients treated with arsenic trioxide for relapsed or refractory APL, with ages ranging from 4 to 21 years. No differences in efficacy and safety were observed by age.

8.5 Geriatric Use

Use of TRISENOX in combination with tretinoin in newly-diagnosed adult patients with low-risk APL is supported by a randomized, controlled trial that included 16 patients between the ages of 60 and 70 years. No overall differences in safety or effectiveness were observed between these patients and younger patients. A literature review included an additional 77 patients aged 60 to 84 years who were treated with arsenic trioxide in combination with tretinoin as part of induction and consolidation therapy for low- and high-risk APL. These studies showed lower survival rates in older patients. Monitor elderly patients frequently during treatment with TRISENOX.

Use of TRISENOX as monotherapy in patients with relapsed or refractory APL is supported by the open-label, single-arm trial that included 6 patients aged 65 and older (range: 65 to 73 years). A literature review included an additional 4 patients aged 69 to 72 years who were treated with arsenic trioxide for relapsed or refractory APL. No overall differences in safety or effectiveness were observed between these patients and younger patients.

8.6 Renal Impairment

Exposure of arsenic trioxide may be higher in patients with severe renal impairment [see Clinical Pharmacology (12.3)]. Monitor patients with severe renal impairment (creatinine clearance [CLcr] less than 30 mL/min) frequently for toxicity; a dose reduction may be warranted.

The use of TRISENOX in patients on dialysis has not been studied.

8.7 Hepatic Impairment

Since limited data are available across all hepatic impairment groups, caution is advised in the use of TRISENOX in patients with hepatic impairment [see Clinical Pharmacology (12.3)]. Monitor patients with severe hepatic impairment (Child-Pugh Class C) frequently for toxicity.

10 OVERDOSAGE

Manifestations

Manifestations of TRISENOX (arsenic trioxide) overdosage include convulsions, muscle weakness, and confusion.

Management

For symptoms of TRISENOX (arsenic trioxide) overdosage, immediately discontinue TRISENOX and consider chelation therapy.

A conventional protocol for acute arsenic intoxication includes dimercaprol administered at a dose of 3 mg/kg intramuscularly every 4 hours until immediate life-threatening toxicity has subsided. Thereafter, penicillamine at a dose of 250 mg orally, up to a maximum frequency of four times per day (≤ 1 g per day), may be given.

11 DESCRIPTION

TRISENOX is a sterile injectable solution of arsenic trioxide. The molecular formula of arsenic trioxide in the solid state is As2O3, with a molecular weight of 197.8 and the following structural formula:

TRISENOX is available in 10 mL, single-dose vials containing 12 mg of arsenic trioxide. TRISENOX is formulated as a sterile, nonpyrogenic, clear solution of arsenic trioxide in water for injection using sodium hydroxide and dilute hydrochloric acid to adjust to pH 8. TRISENOX is preservative-free. Arsenic trioxide, the active ingredient, is present at a concentration of 2 mg/mL. Inactive ingredients and their respective approximate concentrations are sodium hydroxide (1.2 mg/mL) for solubilization, and sodium hydroxide and hydrochloric acid for pH adjustment to pH 8.

12 CLINICAL PHARMACOLOGY

12.1 Mechanism of Action

The mechanism of action of TRISENOX is not completely understood. Arsenic trioxide causes morphological changes and DNA fragmentation characteristic of apoptosis in NB4 human promyelocytic leukemia cells in vitro. Arsenic trioxide also causes damage or degradation of the fusion protein promyelocytic leukemia (PML)-retinoic acid receptor (RAR)-alpha.

12.2 Pharmacodynamics

Cardiac Electrophysiology

In a single-arm trial of TRISENOX (0.15 mg/kg daily), 16 of 40 patients (40%) had a QTc interval greater than 500 msec. Prolongation of the QTc was observed between 1 and 5 weeks after TRISENOX infusion, and then returned towards baseline by the end of 8 weeks after TRISENOX infusion.

12.3 Pharmacokinetics

The inorganic, lyophilized form of arsenic trioxide, when placed into solution, immediately forms the hydrolysis product arsenious acid (AsIII). AsIII is the pharmacologically active species of arsenic trioxide. Monomethylarsonic acid (MMAV), and dimethylarsinic acid (DMAV) are the main pentavalent metabolites formed during metabolism, in addition to arsenic acid (AsV) a product of AsIII oxidation.

The pharmacokinetics of arsenical species ([AsIII], [AsV], [MMAV], [DMAV]) were determined in 6 APL patients following once-daily doses of 0.15 mg/kg for 5 days per week. Over the total single-dose range of 7 to 32 mg (administered as 0.15 mg/kg), systemic exposure (AUC) appears to be linear.

Peak plasma concentrations of arsenious acid (AsIII), the primary active arsenical species were reached at the end of infusion (2 hours). Plasma concentration of AsIII declined in a biphasic manner with a mean elimination half-life of 10 to 14 hours and is characterized by an initial rapid distribution phase followed by a slower terminal elimination phase. The daily exposure to AsIII (mean AUC0-24h) was 194 ng·hr/mL (n=5) on Day 1 of Cycle 1 and 332 ng·hr/mL (n=6) on Day 25 of Cycle 1, which represents an approximate 2-fold accumulation.

The primary pentavalent metabolites, MMAV and DMAV, are slow to appear in plasma (approximately 10 to 24 hours after first administration of arsenic trioxide), but, due to their longer half-life, accumulate more upon multiple dosing than does AsIII. The mean estimated terminal elimination half-lives of the metabolites MMAV and DMAV are 32 hours and 72 hours, respectively. Approximate accumulation ranged from 1.4- to 8-fold following multiple dosing as compared to single-dose administration. AsV is present in plasma only at relatively low levels.

Distribution

The volume of distribution (Vss) for AsIII is large (mean 562 L, N=10) indicating that AsIII is widely distributed throughout body tissues. Vss is also dependent on body weight and increases as body weight increases.

Elimination

Metabolism

Much of the AsIII is distributed to the tissues where it is methylated to the less cytotoxic metabolites, monomethylarsonic acid (MMAV) and dimethylarsinic acid (DMAV) by methyltransferases primarily in the liver. The metabolism of arsenic trioxide also involves oxidation of AsIII to AsV, which may occur in numerous tissues via enzymatic or nonenzymatic processes. AsV is present in plasma only at relatively low levels following administration of arsenic trioxide.

Excretion

Approximately 15% of the administered TRISENOX dose is excreted in the urine as unchanged AsIII. The methylated metabolites of AsIII (MMAV, DMAV) are primarily excreted in the urine. The total clearance of AsIII is 49 L/h and the renal clearance is 9 L/h. Clearance is not dependent on body weight or dose administered over the range of 7 to 32 mg.

Specific Populations

Patients with Renal Impairment

The effect of renal impairment on the pharmacokinetics of AsIII, AsV, and the pentavalent metabolites MMAV and DMAV was evaluated in 20 patients with advanced malignancies. Patients were classified as having normal renal function (creatinine clearance [CLcr] > 80 mL/min, n=6), mild renal impairment (CLcr 50 to 80 mL/min, n=5), moderate renal impairment (CLcr 30 to 49 mL/min, n=6), or severe renal impairment (CLcr < 30 mL/min, n=3). Following twice-weekly administration of 0.15 mg/kg over a 2-hour infusion, the mean AUC0-INF for AsIII was comparable among the normal, mild and moderate renal impairment groups. However, in the severe renal impairment group, the mean AUC0-INF for AsIII was approximately 48% higher than that in the normal group.

Systemic exposure to MMAV and DMAV tended to be larger in patients with renal impairment; however, the clinical consequences of this increased exposure are not known. AsV plasma levels were generally below the limit of assay quantitation in patients with impaired renal function [see Use in Specific Populations (8.6)]. The use of arsenic trioxide in patients on dialysis has not been studied.

Patients with Hepatic Impairment

The effect of pharmacokinetics of AsIII, AsV, and the pentavalent metabolites MMAV and DMAV was evaluated following administration of 0.25 to 0.50 mg/kg of arsenic trioxide in patients with hepatocellular carcinoma. Patients were classified as having normal hepatic function (n=4), mild hepatic impairment (Child-Pugh class A, n=12), moderate hepatic impairment (Child-Pugh class B, n=3), or severe hepatic impairment (Child-Pugh class C, n=1). No clear trend toward an increase in systemic exposure to AsIII, AsV, MMAV or DMAV was observed with decreasing level of hepatic function as assessed by dose-normalized (per mg dose) AUC in the mild and moderate hepatic impairment groups. However, the one patient with severe hepatic impairment had mean dose-normalized AUC0‑24h and Cmax values 40% and 70% higher, respectively, than those patients with normal hepatic function. The mean dose-normalized trough plasma levels for both MMAV and DMAV in this severely hepatically impaired patient were 2.2-fold and 4.7-fold higher, respectively, than those in the patients with normal hepatic function [see Use in Specific Populations (8.7)].

Pediatric Patients

Following intravenous administration of 0.15 mg/kg/day of arsenic trioxide in 10 APL patients (median age = 13.5 years, range 4-20 years), the daily exposure to AsIII (mean AUC0-24h) was 317 ng·hr/mL on Day 1 of Cycle 1 [see Use in Specific Populations (8.4)].

Drug Interaction Studies

No formal assessments of pharmacokinetic drug-drug interactions between TRISENOX and other drugs have been conducted. The methyltransferases responsible for metabolizing arsenic trioxide are not members of the cytochrome P450 family of isoenzymes. In vitro incubation of arsenic trioxide with human liver microsomes showed no inhibitory activity on substrates of the major cytochrome P450 (CYP) enzymes such as 1A2, 2A6, 2B6, 2C8, 2C9, 2C19, 2D6, 2E1, 3A4/5, and 4A9/11. The pharmacokinetics of drugs that are substrates for these CYP enzymes are not expected to be affected by concomitant treatment with arsenic trioxide.

13 NONCLINICAL TOXICOLOGY

13.1 Carcinogenesis, Mutagenesis, Impairment of Fertility

Carcinogenicity studies have not been conducted with TRISENOX [see Warnings and Precautions (5.6)].

Arsenic trioxide and trivalent arsenite salts have not been demonstrated to be mutagenic to bacteria, yeast, or mammalian cells. Arsenite salts are clastogenic in vitro (human fibroblast, human lymphocytes, Chinese hamster ovary cells, Chinese hamster V79 lung cells). Trivalent arsenic was genotoxic in the chromosome aberrations assay and micronucleus bone marrow assay in mice.

The effect of arsenic on fertility has not been adequately studied in humans. Decreased testicular weight and impaired spermatogenesis have been reported in animal studies. Male Wistar rat pups were administered 1.5 mg/kg sodium arsenite solution via the intraperitoneal route from postnatal days 1 to 14 and testes were collected for evaluation on postnatal days 15, 21, and 50. Results of this study revealed an altered morphology of the seminiferous tubules along with degeneration of spermatogenic cells, increased number of sperm with abnormal morphology, and decreased sperm counts. In beagle dogs administered intravenous arsenic trioxide for 90 days, reduced inner cell layers within seminiferous tubules and significantly decreased numbers of spermatocytes, spermatozoa, and sperm cells were observed at doses of 1 mg/kg/day and higher. The 1 mg/kg/day dose is approximately 3 times the recommended human daily dose on a mg/m² basis.

14 CLINICAL STUDIES

14.1 Newly-Diagnosed Low-Risk APL

TRISENOX in combination with tretinoin was investigated in Study APL0406 (NCT00482833), a multicenter, randomized, open-label trial in patients with newly-diagnosed low-risk APL (white blood cell count at diagnosis ≤10 Gi/L). The patients were randomized 1:1 to receive TRISENOX/tretinoin for induction and consolidation or chemotherapy/tretinoin for induction, consolidation, and maintenance.

Patients in the TRISENOX/tretinoin group received induction treatment with TRISENOX 0.15 mg/kg intravenously once daily in combination with tretinoin 22.5 mg/m^2 (rounded to the nearest 10 mg increment) orally twice daily until hematologic complete remission (CR) or for a maximum of 60 days. Patients in this group who achieved a CR during induction received four 8-week cycles of consolidation treatment with TRISENOX 0.15 mg/kg intravenously once daily for 5 days every week during weeks 1 to 4 of the 8-week cycle, in combination with tretinoin 22.5 mg/m^2 (rounded to the nearest 10 mg increment) orally twice daily during weeks 1 to 2 and 5 to 6 of the 8-week cycle. Tretinoin was omitted during weeks 5 to 6 of the last cycle.

Patients in the chemotherapy/tretinoin group received idarubicin 12 mg/m^2 intravenously once daily on days 2, 4, 6, and 8 in combination with tretinoin 22.5 mg/m^2 (rounded to the nearest 10 mg increment) orally twice daily, starting on day 1, until hematologic CR or for a maximum of 60 days. Patients in this group who achieved a CR during induction received consolidation and maintenance treatment with tretinoin in combination with chemotherapy.

The trial enrolled 162 patients with a morphologic diagnosis of APL. The median age of patients was 45 years in the TRISENOX/tretinoin arm and 47 years in the chemotherapy/tretinoin arm, and 52% and 46% were male in the TRISENOX/tretinoin and chemotherapy/tretinoin arms, respectively. Baseline characteristics were balanced between treatment arms, including median WBC count, platelet count, PML-RARA isoform, and FLT3-ITD status.

Efficacy was based on event-free survival (EFS) rate at 2 years. EFS was defined as the time from randomization to the occurrence of treatment failure, defined as no achievement of CR or CRi after induction therapy, no achievement of molecular remission after 3 consolidation courses, molecular relapse, hematologic relapse, or death. The primary analysis of EFS was based on the difference between the two treatment arms in patients achieving EFS at 2 years. With a median follow-up of 34.4 months, the 2 year EFS rate of the modified ITT (mITT) population (patients who received at least one dose of the assigned treatment) was 94% in the TRISENOX/tretinoin arm (n=77) versus 82% in the chemotherapy/tretinoin arm (n=79), a treatment difference of 11% (95% CI: 1, 22; p-value 0.048). Overall survival (OS) for the mITT population was 99% (95% CI: 93, 100) in the TRISENOX/tretinoin arm versus 91% (95% CI: 86, 97) in the chemotherapy/tretinoin arm. The difference in 2-year OS rate between the arms was 8% (95% CI: 0, 16).

The number of patients in the plot is based on the mITT population.

14.2 Relapsed or Refractory APL

TRISENOX was investigated in Study PLRXAS01, an open-label, single-arm trial in 40 patients with relapsed or refractory APL who were previously treated with an anthracycline and a retinoid regimen. Patients received TRISENOX 0.15 mg/kg/day intravenously over 1 to 2 hours until the bone marrow was cleared of leukemic cells or for a maximum of 60 days. The CR (absence of visible leukemic cells in bone marrow and peripheral recovery of platelets and white blood cells with a confirmatory bone marrow ≥ 30 days later) rate in this population of previously treated patients was 28 of 40 (70%). Among the 22 patients who had relapsed less than one year after treatment with tretinoin, there were 18 complete responders (82%). Of the 18 patients receiving TRISENOX ≥ one year from tretinoin treatment, there were 10 complete responders (55%). The median time to bone marrow remission was 44 days and to onset of CR was 53 days. Three of 5 children, 5 years or older, achieved CR. No children less than 5 years old were treated.

Three to six weeks following bone marrow remission, 31 patients received consolidation therapy with TRISENOX, at the same dose, for 25 additional days over a period up to 5 weeks. In follow-up treatment, 18 patients received further TRISENOX as a maintenance course. Fifteen patients had bone marrow transplants. At last follow-up, 27 of 40 patients were alive with a median follow-up time of 484 days (range 280 to 755) and 23 of 40 patients remained in complete response with a median follow-up time of 483 days (range 280 to 755).

Cytogenetic conversion to no detection of the APL chromosome rearrangement was observed in 24 of 28 (86%) patients who met the response criteria defined above, in 5 of 5 (100%) patients who met some, but not all, of the response criteria, and 3 of 7 (43%) of patients who did not respond. RT-PCR conversions to no detection of the APL gene rearrangement were demonstrated in 22 of 28 (79%) of patients who met the response criteria, in 3 of 5 (60%) of patients who met some, but not all, of the response criteria, and in 2 of 7 (29%) of patients who did not respond.

Responses were seen across all age groups tested, ranging from 6 to 72 years. The ability to achieve a CR was similar for both sexes. There were insufficient patients of Black, Hispanic, or Asian ancestry to estimate relative response rates in these groups, but responses were seen in each group.

15 REFERENCES

1. “OSHA Hazardous Drugs.” OSHA. http://www.osha.gov/SLTC/hazardousdrugs/index.html

16 HOW SUPPLIED/STORAGE AND HANDLING

How Supplied

TRISENOX (arsenic trioxide) injection is supplied as a sterile, clear, colorless solution in 10 mL glass, single-dose vials.

NDC 63459-601-06: 12 mg/6 mL (2 mg/mL) vial in packages of ten vials.

Storage and Handling

Store at 20°C to 25°C (68°F to 77°F); excursions permitted to 15°C to 30°C (59°F to 86°F) [See USP Controlled Room Temperature]. Do not freeze.

TRISENOX is a hazardous drug. Follow applicable special handling and disposal procedures.^1

17 PATIENT COUNSELING INFORMATION

Differentiation Syndrome
Advise patients that symptoms of APL differentiation syndrome include fever, sudden weight gain, dizziness/lightheadedness, labored breathing, and accumulation of fluid in the lungs, heart, and chest. This syndrome is managed by immediate treatment with high-dose corticosteroids. Advise patients to immediately report any of these symptoms [see Warnings and Precautions (5.1)].

Cardiac Conduction Abnormalities
Advise patients that TRISENOX may cause ECG abnormalities, including QT prolongation. If extreme, this prolongation has the potential to cause fainting, irregular heartbeat, or more serious side effects. Advise patients to immediately report any of these symptoms. Advise patients to provide a complete list of current medications as caution should be taken when TRISENOX is coadministered with other medications that can cause QT prolongation or lead to electrolyte abnormalities [see Warnings and Precautions (5.2) and Drug Interactions (7)].

Encephalopathy and Wernicke's Encephalopathy (WE)

Advise patients that symptoms of encephalopathies include neurological symptoms such as confusion, decreased level of consciousness, seizures, cognitive deficits, ataxia, visual symptoms and ocular motor dysfunction. Advise patients and caregivers to closely monitor for neurological symptoms and immediately report them to their healthcare provider [see Warnings and Precautions (5.3)].

Advise patients at risk for thiamine deficiency (e.g., chronic alcohol use, malabsorption, nutritional deficiency, concomitant use of furosemide) that Wernicke’s encephalopathy is a neurologic emergency that can be prevented and treated with thiamine supplementation, and to immediately report any neurological symptoms to their healthcare provider [see Warnings and Precautions (5.3)].

Embryo-Fetal Toxicity
Advise pregnant women of the potential risk to a fetus. Advise females of reproductive potential to inform their healthcare provider of a known or suspected pregnancy [see Warnings and Precautions (5.5) and Use in Specific Populations 8.1)].

Advise females of reproductive potential to use effective contraception during treatment with TRISENOX and for 6 months after the last dose [see Use in Specific Populations (8.3)].

Advise males with female partners of reproductive potential to use effective contraception during treatment with TRISENOX for 3 months after the last dose [see Use in Specific Populations (8.3)].

Lactation
Advise women not to breastfeed during treatment with TRISENOX and for 2 weeks after the last dose [see Use in Specific Populations (8.2)].

Infertility

Advise males of reproductive potential that TRISENOX may impair fertility [see Use in Specific Population (8.3)].

Other Adverse Reactions
Advise patients of the expected adverse reactions of TRISENOX. Most patients in clinical trials experienced some drug-related toxicity, most commonly leukocytosis, gastrointestinal symptoms (nausea, vomiting, diarrhea, and abdominal pain), fatigue, edema, hyperglycemia, dyspnea, cough, rash or itching, headaches, and dizziness. Advise patients to call their healthcare provider at the onset of any adverse reactions [see Adverse Reactions (6.1)].

Manufactured for:
Teva Pharmaceuticals
Parsippany, NJ 07054

©2022 Teva Pharmaceuticals, Inc.

Rev. 6/2022

TRI-015

Package/Label Display Panel

NDC 63459-601-06

Trisenox® (arsenic trioxide)

injection

12 mg/6 mL (2 mg/mL)

10 x 6 mL

Single-Dose Vial – Discard Unused Portion

For Intravenous Use Only

10 x 6 mL

Single-Dose Vial

Rx only

Teva